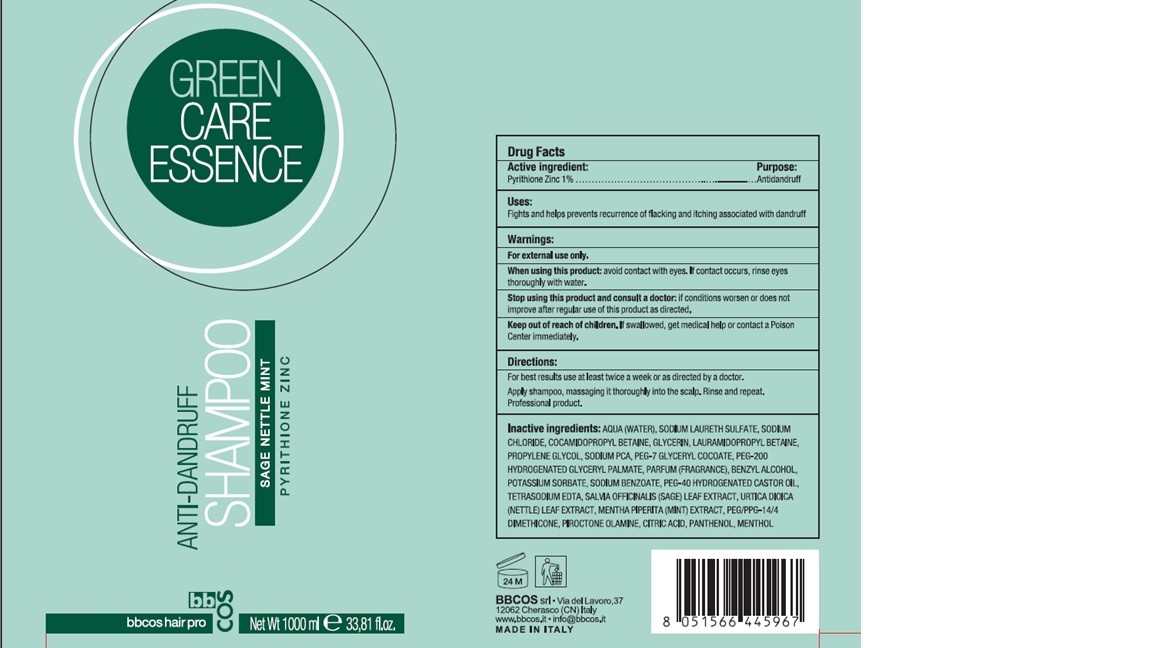 DRUG LABEL: ANTIDANDRUFF
NDC: 70549-123 | Form: SHAMPOO
Manufacturer: BBCOS S.R.L.
Category: otc | Type: HUMAN OTC DRUG LABEL
Date: 20160519

ACTIVE INGREDIENTS: PYRITHIONE ZINC 10 mg/1000 mg
INACTIVE INGREDIENTS: POLYOXYL 40 HYDROGENATED CASTOR OIL; CITRIC ACID MONOHYDRATE; WATER; SODIUM LAURETH SULFATE; SODIUM CHLORIDE; COCAMIDOPROPYL BETAINE; GLYCERIN; LAURAMIDOPROPYL BETAINE; PROPYLENE GLYCOL; SODIUM PYRROLIDONE CARBOXYLATE; PEG-7 GLYCERYL COCOATE; PEG-200 HYDROGENATED GLYCERYL PALMATE; EDETATE SODIUM; BENZYL ALCOHOL; POTASSIUM SORBATE; SODIUM BENZOATE; PEG/PPG-14/4 DIMETHICONE; PIROCTONE OLAMINE; PANTHENOL; MENTHOL; SAGE; URTICA DIOICA LEAF; MENTHA PIPERITA

GREEN CARE ESSENCE ANTI-DANDRUFF SHAMPOO
These highlights do not include all the information needed to use see full prescribing information for Initial U.S. Approval

Active Ingredient:

Pyrithione Zinc 1%

Uses:

Fights and helps prevents recurrence of flacking and itching associated with dandruff

Warnings:

For external use only.

When using this product:

avoid contact with eyes. If contact occurs, rinse eyes thoroughly with water.

Stop using this product and consult a doctor:

if conditions worsen or does not improve after regular use of this product as directed.

Keep out of reach of children.

If swallowed, get medical help or contact a Poison Center immediately.

Directions:

For best results use at least twice a week or as directed by a dcoctor.

INDICATIONS AND USAGE

Apply shampoo, massaging it thoroughly into the scalp. Rinse and repeat.

Professional product.

Inactive ingredients:

AQUA (WATER), SODIUM LAURETH SULFATE, SODIUM CHLORIDE, COCAMIDOPROPYL BETAINE, GLYCERIN, LAURAMIDOPROPYL BETAINE, PROPYLENE GLYCOL, SODIUM PCA, PEG-7 GLYCERYL COCOATE, PEG-200 HYDROGENATED GLYCERYL PALMATE, PARFUM (FRAGRANCE), BENZYL ALCHOL, POTASSIUM SORBATE, SODIUM BENZOATE, PEG-40 HYDROGENATED CASTOR OIL, TETRASODIUM EDTA, SALVIA OFFICINALIS (SAGE) LEAF EXTRACT, URTICA DIOICA (NETTLE) LEAF EXTRACT, MENTHA PIPERITA (MINT) EXTRACT, PEG/PPG-14/4 DIMETHICONE, PIROCTONE OLAMINE, CITRIC ACID, PANTHENOL, MENTHOL

PACKAGE LABEL

GREEN

CARE

ESSENCE

ANTI-DANDRUFF

SHAMPOO

SAGE NETTLE MINT

PYRITHIONE ZINC